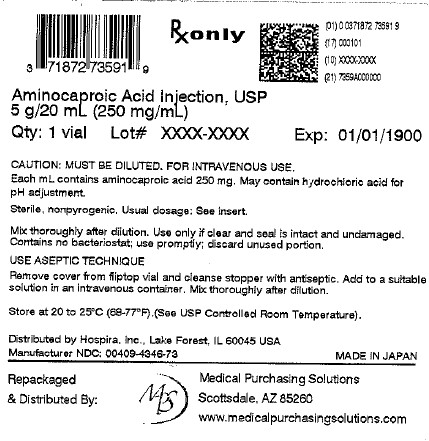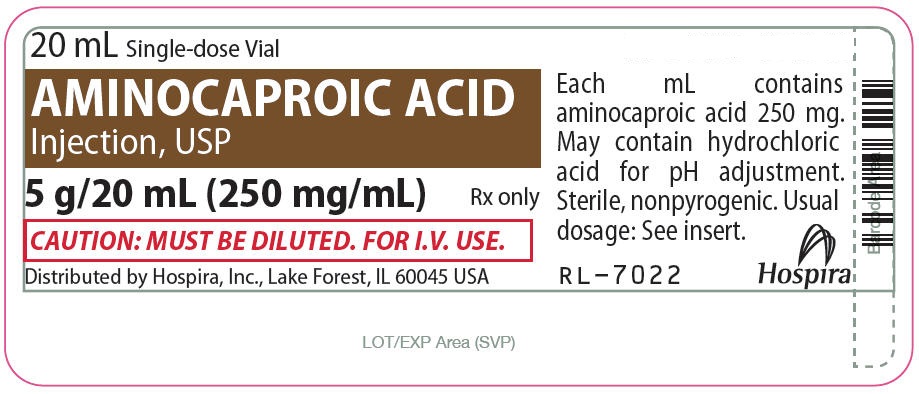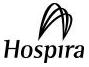 DRUG LABEL: Aminocaproic Acid
NDC: 71872-7359 | Form: INJECTION, SOLUTION
Manufacturer: Medical Purchasing Solutions, LLC
Category: prescription | Type: HUMAN PRESCRIPTION DRUG LABEL
Date: 20251217

ACTIVE INGREDIENTS: AMINOCAPROIC ACID 250 mg/1 mL
INACTIVE INGREDIENTS: WATER; HYDROCHLORIC ACID

AMINOCAPROIC ACID
Injection, USP

5 g/20 mL (250 mg/mL)

Plastic Fliptop Vial

Rxonly

DESCRIPTION

Aminocaproic Acid Injection, USP is a 6-aminohexanoic acid, which acts as an inhibitor of fibrinolysis.

Aminocaproic Acid is soluble in water, acid and alkaline solutions; it is sparingly soluble in methanol and practically insoluble in chloroform.

Aminocaproic Acid Injection, USP, for intravenous administration, is a sterile pyrogen-free solution containing 250 mg/mL of aminocaproic acid and Water for Injection. The solution contains no bacteriostat or antimicrobial agent and is intended for use only as a single-dose injection. When smaller doses are required the unused portion should be discarded. Hydrochloric acid may be added to adjust pH to approximately 6.8 during manufacture.

Its chemical structure is:

NH2- CH2- CH2- CH2- CH2- CH2- COOH

Molecular Weight: 131.17

The semi-rigid vial is fabricated from a specifically formulated polyolefin. It is a copolymer of ethylene and propylene. The safety of the plastic has been confirmed by tests in animals according to USP biological standards for plastic containers. The container requires no vapor barrier to maintain the proper drug concentration.

CLINICAL PHARMACOLOGY

The fibrinolysis-inhibitory effects of aminocaproic acid appear to be exerted principally via inhibition of plasminogen activators and to a lesser degree through antiplasmin activity. In adults, oral absorption appears to be a zero-order process with an absorption rate of 5.2 g/hr. The mean lag time in absorption is 10 minutes. After a single oral dose of 5 g, absorption was complete (F=1). Mean ± SD peak plasma concentrations (164 ± 28 mcg/mL) were reached within 1.2 ± 0.45 hours. After oral administration, the apparent volume of distribution was estimated to be 23.1± 6.6 L (mean ± SD). Correspondingly, the volume of distribution after intravenous administration has been reported to be 30 ± 8.2 L. After prolonged administration, aminocaproic acid has been found to distribute throughout extravascular and intravascular compartments of the body, penetrating human red blood cells as well as other tissue cells.

Renal excretion is the primary route of elimination, whether aminocaproic acid is administered orally or intravenously. Sixty-five percent of the dose is recovered in the urine as unchanged drug and 11% of the dose appears as the metabolite adipic acid. Renal clearance (116 mL/min) approximates endogenous creatinine clearance. The total body clearance is 169 mL/min. The terminal elimination half-life for aminocaproic acid is approximately 2 hours.

INDICATIONS AND USAGE

Aminocaproic Acid Injection, is useful in enhancing hemostasis when fibrinolysis contributes to bleeding. In life-threatening situations, fresh whole blood transfusions, fibrinogen infusions, and other emergency measures may be required.

Fibrinolytic bleeding may frequently be associated with surgical complications following heart surgery (with or without cardiac bypass procedures), and portacaval shunt; hematological disorders such as aplastic anemia; acute and life-threatening abruptio placentae; hepatic cirrhosis; and neoplastic disease such as carcinoma of the prostate, lung, stomach, and cervix.

Urinary fibrinolysis, usually a normal physiological phenomenon, may frequently be associated with life-threatening complications following severe trauma, anoxia, and shock. Symptomatic of such complications is surgical hematuria (following prostatectomy and nephrectomy) or nonsurgical hematuria (accompanying polycystic or neoplastic diseases of the genitourinary system). (See WARNINGS.)

CONTRAINDICATIONS

Aminocaproic acid should not be used when there is evidence of an active intravascular clotting process.

When there is uncertainty as to whether the cause of bleeding is primary fibrinolysis or disseminated intravascular coagulation (DIC), this distinction must be made before administering Aminocaproic Acid Injection.

The following tests can be applied to differentiate the two conditions:

- Platelet count is usually decreased in DIC but normal in primary fibrinolysis.
- Protamine paracoagulation test is positive in DIC; a precipitate forms when protamine sulfate is dropped into citrated plasma. The test is negative in the presence of primary fibrinolysis.
- The euglobulin clot lysis test is abnormal in primary fibrinolysis but normal in DIC.

Aminocaproic Acid Injection must not be used in the presence of DIC without concomitant heparin.

WARNINGS

In patients with upper urinary tract bleeding, aminocaproic acid administration has been known to cause intrarenal obstruction in the form of glomerular capillary thrombosis or clots in the renal pelvis and ureters. For this reason, Aminocaproic Acid Injection, USP should not be used in hematuria of upper urinary tract origin, unless the possible benefits outweigh the risk.

Subendocardial hemorrhages have been observed in dogs given intravenous infusions of 0.2 times the maximum human therapeutic dose of aminocaproic acid and in monkeys given 8 times the maximum human therapeutic dose of aminocaproic acid.

Fatty degeneration of the myocardium has been reported in dogs given intravenous doses of aminocaproic acid at 0.8 to 3.3 times the maximum human therapeutic dose and in monkeys given intravenous doses of aminocaproic acid at 6 times the maximum human therapeutic dose.

Rarely, skeletal muscle weakness with necrosis of muscle fibers has been reported following prolonged administration. Clinical presentation may range from mild myalgias with weakness and fatigue to a severe proximal myopathy with rhabdomyolysis, myoglobinuria, and acute renal failure. Muscle enzymes, especially creatine phosphokinase (CPK) are elevated. CPK levels should be monitored in patients on long-term therapy. Aminocaproic Acid Injection administration should be stopped if a rise in CPK is noted. Resolution follows discontinuation of Aminocaproic Acid Injection; however, the syndrome may recur if Aminocaproic Acid Injection is restarted.

The possibility of cardiac muscle damage should also be considered when skeletal myopathy occurs. One case of cardiacand hepatic lesionsobserved in man has been reported. The patient received 2 g of aminocaproic acid every 6 hours for a total dose of 26 g. Death was due to continued cerebrovascular hemorrhage. Necrotic changes in the heart and liver were noted at autopsy.

PRECAUTIONS

General

Aminocaproic Acid Injection, inhibits both the action of plasminogen activators and to a lesser degree, plasmin activity. The drug should NOT be administered without a definite diagnosis and/or laboratory finding indicative of hyperfibrinolysis (hyperplasminemia).*

Rapid intravenous administration of the drug should be avoided since this may induce hypotension, bradycardia, and/or arrhythmia.

Inhibition of fibrinolysis by aminocaproic acid may theoretically result in clotting or thrombosis. However, there is no definite evidence that administration of aminocaproic acid has been responsible for the few reported cases of intravascular clotting which followed this treatment. Rather, it appears that such intravascular clotting was most likely due to the patient's pre-existing clinical condition, e.g., the presence of DIC. It has been postulated that extravascular clots formed in vivomay not undergo spontaneous lysis as do normal clots.

Reports have appeared in the literature of an increased incidence of certain neurological deficits such as hydrocephalus, cerebral ischemia, or cerebral vasospasm associated with the use of antifibrinolytic agents in the treatment of subarachnoid hemorrhage (SAH). All of these events have also been described as part of the natural course of SAH, or as a consequence of diagnostic procedures such as angiography. Drug relatedness remains unclear.

Thrombophlebitis, a possibility with all intravenous therapy, should be guarded against by strict attention to the proper insertion of the needle and the fixing of its position.

Epsilon-aminocaproic acid should not be administered with Factor IX Complex concentrates or Anti-Inhibitor Coagulant concentrates, as the risk of thrombosis may be increased.

Laboratory Tests

The use of Aminocaproic Acid Injection, USP should be accompanied by tests designed to determine the amount of fibrinolysis present. There are presently available: (a) general tests such as those for the determination of the lysis of a clot of blood or plasma; and (b) more specific tests for the study of various phases of fibrinolytic mechanisms. These latter tests include both semiquantitative and quantitative techniques for the determination of profibrinolysin, fibrinolysin, and antifibrinolysin.

Drug Laboratory Test Interactions

Prolongation of the template bleeding time has been reported during continuous intravenous infusion of Aminocaproic Acid Injection at dosages exceeding 24 g/day. Platelet function studies in these patients have not demonstrated any significant platelet dysfunction. However, in vitrostudies have shown that at high concentrations (7.4 mMol/L or 0.97 mg/mL and greater) EACA inhibits ADP and collagen-induced platelet aggregation, the release of ATP and serotonin, and the binding of fibrinogen to the platelets in a concentration-response manner. Following a 10 g bolus of Aminocaproic Acid Injection, transient peak plasma concentrations of 4.6 mMol/L or 0.60 mg/mL have been obtained. The concentration of aminocaproic acid necessary to maintain inhibition of fibrinolysis is 0.99 mMol/L or 0.13 mg/mL. Administration of a 5 g bolus followed by 1 to 1.25 g/hr should achieve and sustain plasma levels of 0.13 mg/mL. Thus, concentrations which have been obtained in vivoclinically in patients with normal renal function are considerably lower than the in vitroconcentrations found to induce abnormalities in platelet function tests. However, higher plasma concentrations of aminocaproic acid may occur in patients with severe renal failure.

Carcinogenesis, Mutagenesis, Impairment of Fertility

Long-term studies in animals to evaluate the carcinogenic potential of aminocaproic acid and studies to evaluate its mutagenic potential have not been conducted. Dietary administration of an equivalent of the maximum human therapeutic dose of aminocaproic acid to rats of both sexes impaired fertility as evidenced by decreased implantations, litter sizes and number of pups born.

Pregnancy

Animal reproduction studies have not been conducted with aminocaproic acid. It is also not known whether aminocaproic acid can cause fetal harm when administered to a pregnant woman or can affect reproduction capacity. Aminocaproic Acid Injection should be given to a pregnant woman only if clearly needed.

Nursing Mothers

It is not known whether this drug is excreted in human milk. Because many drugs are excreted in human milk, caution should be exercised when aminocaproic acid is administered to a nursing woman.

Pediatric Use

Safety and effectiveness in pediatric patients have not been established.

ADVERSE REACTIONS

Aminocaproic Acid Injection is generally well tolerated. The following adverse experiences have been reported:

General: Edema, headache, malaise.

Hypersensitivity Reactions: Allergic and anaphylactoid reactions, anaphylaxis.

Local Reactions: Injection site reactions, pain and necrosis.

Cardiovascular: Bradycardia, hypotension, peripheral ischemia, thrombosis.

Gastrointestinal: Abdominal pain, diarrhea, nausea, vomiting.

Hematologic: Agranulocytosis, coagulation disorder, leukopenia, thrombocytopenia.

Musculoskeletal: CPK increased, muscle weakness, myalgia, myopathy (see WARNINGS), myositis, rhabdomyolysis.

Neurologic: Confusion, convulsions, delirium, dizziness, hallucinations, intracranial hypertension, stroke, syncope.

Respiratory: Dyspnea, nasal congestion, pulmonary embolism.

Skin: Pruritus, rash.

Special Senses: Tinnitus, vision decreased, watery eyes.

Urogenital: BUN increased, renal failure. There have been some reports of dry ejaculation during the period of Aminocaproic Acid Injection treatment. These have been reported to date only in hemophilia patients who received the drug after undergoing dental surgical procedures. However, this symptom resolved in all patients within 24 to 48 hours of completion of therapy.

OVERDOSAGE

A few cases of acute overdosage with Aminocaproic Acid Injection administered intravenously have been reported. The effects have ranged from no reaction to transient hypotension to severe acute renal failure leading to death. One patient with a history of brain tumor and seizures experienced seizures after receiving an 8 gram bolus injection of Aminocaproic Acid Injection. The single dose of Aminocaproic Acid Injection causing symptoms of overdosage or considered to be life-threatening is unknown. Patients have tolerated doses as high as 100 grams while acute renal failure has been reported following a dose of 12 grams.

The intravenous and oral LD50of aminocaproic acid were 3 and 12 g/kg respectively, in the mouse and 3.2 and 16.4 g/kg respectively in the rat. An intravenous infusion dose of 2.3 g/kg was lethal in the dog. On intravenous administration, tonic-clonic convulsions were observed in dogs and mice.

No treatment for overdosage is known, although evidence exists that aminocaproic acid is removed by hemodialysis and may be removed by peritoneal dialysis. Pharmacokinetic studies have shown that total body clearance of aminocaproic acid is markedly decreased in patients with severe renal failure.

DOSAGE AND ADMINISTRATION

Intravenous

Aminocaproic Acid Injection, USP is administered by infusion, utilizing the usual compatible intravenous vehicles (e.g., Sterile Water for Injection, Sodium Chloride for Injection, 5% Dextrose or Ringer’s Injection). Although Sterile Water for Injection is compatible for intravenous injection the resultant solution is hypo-osmolar. RAPID INJECTION OF AMINOCAPROIC ACID INJECTION UNDILUTED INTO A VEIN IS NOT RECOMMENDED.

For the treatment of acute bleeding syndromes due to elevated fibrinolytic activity, it is suggested that 16 to 20 mL (4 to 5 g) of aminocaproic acid in 250 mL of diluent be administered by infusion during the first hour of treatment, followed by a continuing infusion at the rate of 4 mL (1 g) per hour in 50 mL of diluent. This method of treatment would ordinarily be continued for about 8 hours or until the bleeding situation has been controlled.

Parenteral drug products should be inspected visually for particulate matter and discoloration prior to administration, whenever solution and container permit. Do not administer unless the solution is clear and seal is intact. Discard unused portion.

HOW SUPPLIED

Aminocaproic Acid Injection, USP is supplied in single-dose containers as follows:

Unit of Sale | Concentration
NDC 0409-4346-73 Tray containing 25 Single-dose (20 mL in 30 mL) Fliptop Vials | 5 g/20 mL (250 mg/mL)

Store at 20 to 25°C (68 to 77°F). [See USP Controlled Room Temperature.]

References

* Stefanini, M. and Dameshek, W.: The Hemorrhagic Disorder, Ed. 2, New York. Grune and Stratton, pp. 510-514, 1962.

Distributed by Hospira, Inc., Lake Forest, IL 60045 USA

LAB-0948-3.0

Revised: 6/2018

PRINCIPAL DISPLAY PANEL - VIAL LABEL

20 mL Single-dose Vial

AMINOCAPROIC ACID
Injection, USP

5 g/20 mL (250 mg/mL)
Rx only

CAUTION: MUST BE DILUTED. FOR I.V. USE.

PRINCIPAL DISPLAY PANEL - OUTER PACKAGE

NDC 71872-7359-1

Aminocaproic Acid Injection, USP

5 g/20 mL (250 mg/mL)

1 x 20 mL Single-dose Vial
Rx only

CAUTION:
MUST BE DILUTED.
FOR INTRAVENOUS USE.